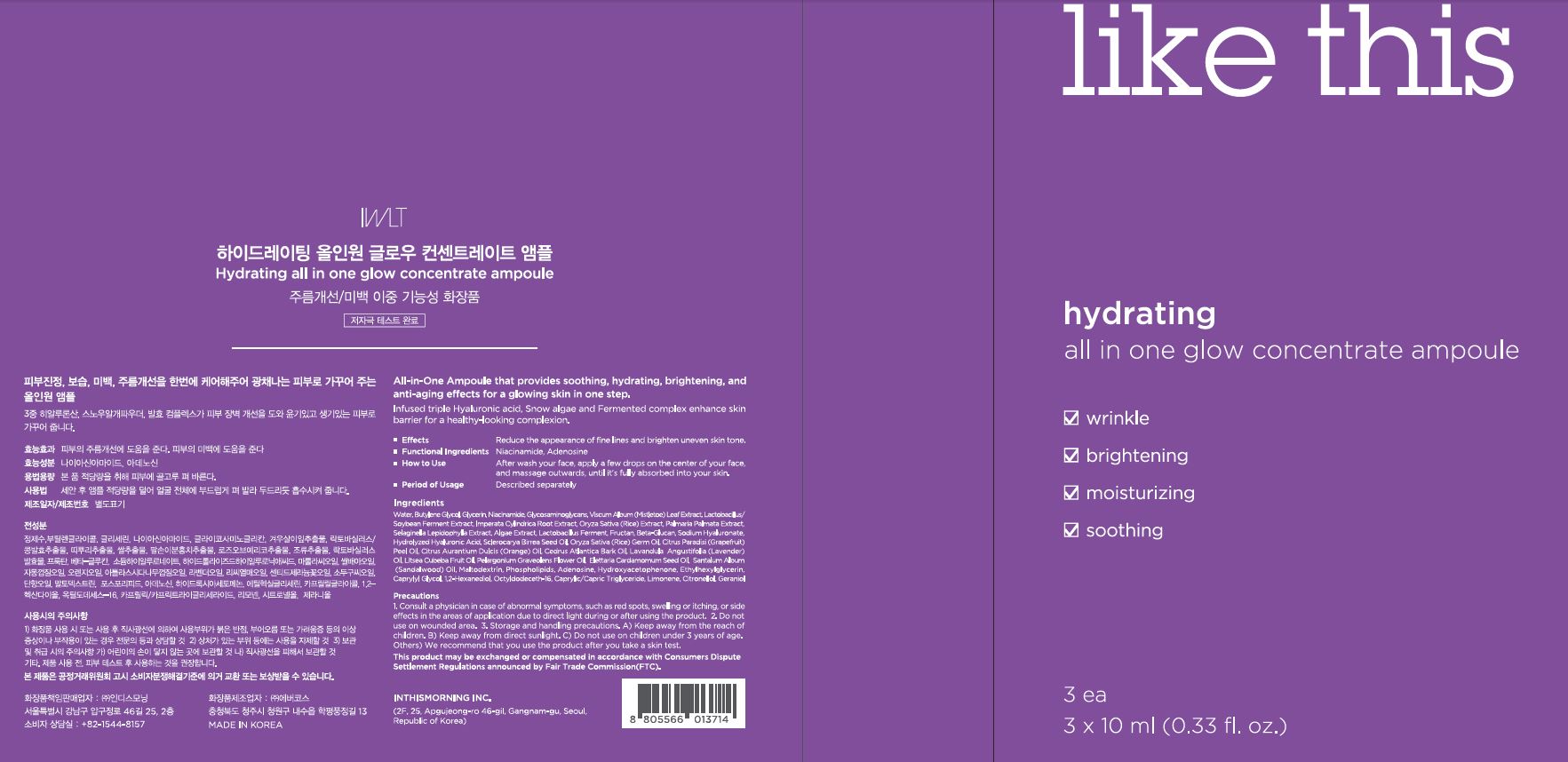 DRUG LABEL: Hydrating all in one glow concentrate ampoule
NDC: 71217-0051 | Form: LIQUID
Manufacturer: inthismorning co ltd
Category: otc | Type: HUMAN OTC DRUG LABEL
Date: 20230201

ACTIVE INGREDIENTS: NIACINAMIDE 2 g/100 mL; ADENOSINE 0.04 g/100 mL
INACTIVE INGREDIENTS: WATER

Drug Facts

ACTIVE INGREDIENT

niacinamide, adenosine

INACTIVE INGREDIENT

water, glycerin, etc.

PURPOSE

wrinkle care, brightening, moisturizing, soothing

keep out or reach of the children

INDICATIONS AND USAGE

after wasj upir face. a[[;u a few drops on the center of your face, and massage outwards until it's fully absorbed into your skin

WARNINGS

This product is for exeternal use only. Do not use for internal use
Storage and handling precautions
If possible, avoid direct sunlight and store in cool and area of low humidity in order to maintain the quality of the product and avoid misuse
Avoid placing the product near fire and store out in reach of children

- consult a physician in case of abnormal symptoms, such as red spots, swelling or itching, or side effects in the areas of application due to direct light during or after using the product

- do not use on wounded area

DOSAGE AND ADMINISTRATION

for external use only